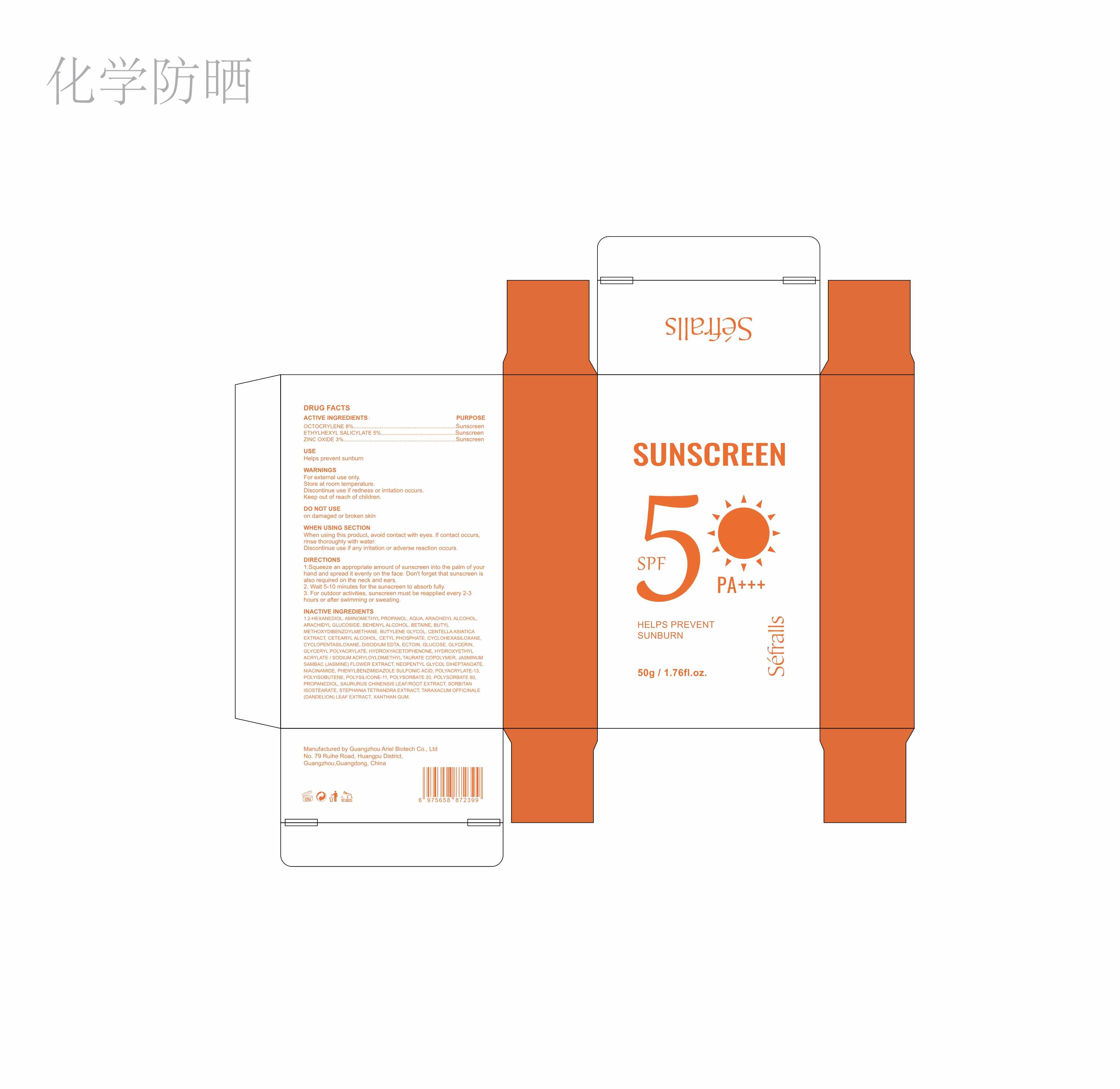 DRUG LABEL: Sunscreen SPF 50
NDC: 84148-002 | Form: CREAM
Manufacturer: Guangzhou Ariel Biotech Co., Ltd.
Category: otc | Type: HUMAN OTC DRUG LABEL
Date: 20240328

ACTIVE INGREDIENTS: OCTOCRYLENE 8 g/100 g; ZINC OXIDE 3 g/100 g; OCTISALATE 5 g/100 g
INACTIVE INGREDIENTS: POLYSORBATE 20; HYDROXYACETOPHENONE; PROPANEDIOL; CETYL PHOSPHATE; CETOSTEARYL ALCOHOL; ARACHIDYL ALCOHOL; ECTOINE; TARAXACUM OFFICINALE; BETAZINE; HYDROXYETHYL ACRYLATE/SODIUM ACRYLOYLDIMETHYL TAURATE COPOLYMER (45000 MPA.S AT 1%); ENSULIZOLE; POLYISOBUTYLENE (1000 MW); EDETATE DISODIUM; AVOBENZONE; GLYCERIN; POLYSORBATE 60; ARACHIDYL GLUCOSIDE; DOCOSANOL; JASMINUM SAMBAC FLOWER; DIMETHICONE/VINYL DIMETHICONE CROSSPOLYMER (SOFT PARTICLE); SORBITAN ISOSTEARATE; NIACINAMIDE; CYCLOMETHICONE 7; BUTYLENE GLYCOL; CENTELLA ASIATICA TRITERPENOIDS; NEOPENTYL GLYCOL DIHEPTANOATE; POLYACRYLATE-13; STEPHANIA TETRANDRA WHOLE; XANTHAN GUM; 1,2-HEXANEDIOL; WATER; AMINOMETHYLPROPANOL; CYCLOMETHICONE 6; ANHYDROUS DEXTROSE; SAURURUS CHINENSIS FLOWER

84148-002

ACTIVE INGREDIENTS :

ACTIVE INGREDIENTSPURPOSEOCTOCRYLENE8%…………Sunscreen

ETHYLHEXYL SALICYLATE 5%.…………Sunscreen

ZINC OXIDE 3%.....Sunscreen

Use:

Helps prevent sunburn

Warnings:

WARNINGSFor external use only.Store at room temperatureDiscontinue use if redness or irritation occurs

DO NOT USE
on damaged or broken skin

WHEN USING SECTION:

When using this product, avoid contact with eyes. lf contact occurs, rinse thoroughly with water.

Discontinue use if any irritation or adverse reaction occurs.

INSTRUCTIONS FOR USE

WHEN USING SECTION
When using this product, avoid contact with eyes. lf contact occursrinse thoroughly with water.
Discontinue use if any irritation or adverse reaction occurs

INACTIVE INGREDIENTS
1,2-HEXANEDIOL, AMINOMETHYL PROPANOL, AQUA, ARACHIDYL ALCOHOLARACHIDYL GLUCOSIDE, BEHENYL ALCOHOL, BETAINE, BUTYLMETHOXYDIBENZOYLMETHANE, BUTYLENE GLYCOL, CENTELLA ASIATICAEXTRACT, CETEARYL ALCOHOL, CETYL PHOSPHATE, CYCLOHEXASILOXANECYCLOPENTASILOXANE, DISODIUM EDTA, ECTOIN, GLUCOSE, GLYCERIN,GLYCERYL POLYACRYLATE, HYDROXYACETOPHENONE, HYDROXYETHYLACRYLATE / SODIUM ACRYLOYLDIMETHYL TAURATE COPOLYMER, JASMINUMSAMBAC (JASMINE) FLOWER EXTRACT, NEOPENTYL GLYCOL DIHEPTANOATENIACINAMIDE, PHENYLBENZIMIDAZOLE SULFONIC ACID, POLYACRYLATE-13.POLYISOBUTENE, POLYSILICONE-11, POLYSORBATE 20, POLYSORBATE 60.PROPANEDIOL, SAURURUS CHINENSIS LEAF/ROOT EXTRACT, SORBITANISOSTEARATE, STEPHANIA TETRANDRA EXTRACT, TARAXACUM OFFICINALE(DANDELION) LEAF EXTRACT, XANTHAN GUM.

OTHER SAFETY INFORMATION

Manufactured by Guangzhou Ariel Biotech Co., Ltd

No. 79 Ruihe Road, Huangpu District, Guangzhou,Guangdong, China

PURPOSE

Sunscreen

DIRECTIONS
1.Squeeze an appropriate amount of sunscreen into the palm of yourhand and spread it evenly on the face. Don't forget that sunscreen isalso required on the neck and ears.2. Wait 5-10 minutes for the sunscreen to absorb fully.3. For outdoor activities, sunscreen must be reapplied every 2-3hours or after swimming or sweating.

Keep out of reach of children.

INDICATIONS AND USAGE

WHEN USING SECTION
When using this product, avoid contact with eyes. lf contact occurs.
rinse thoroughly with water.
Discontinue use if any irritation or adverse reaction occurs